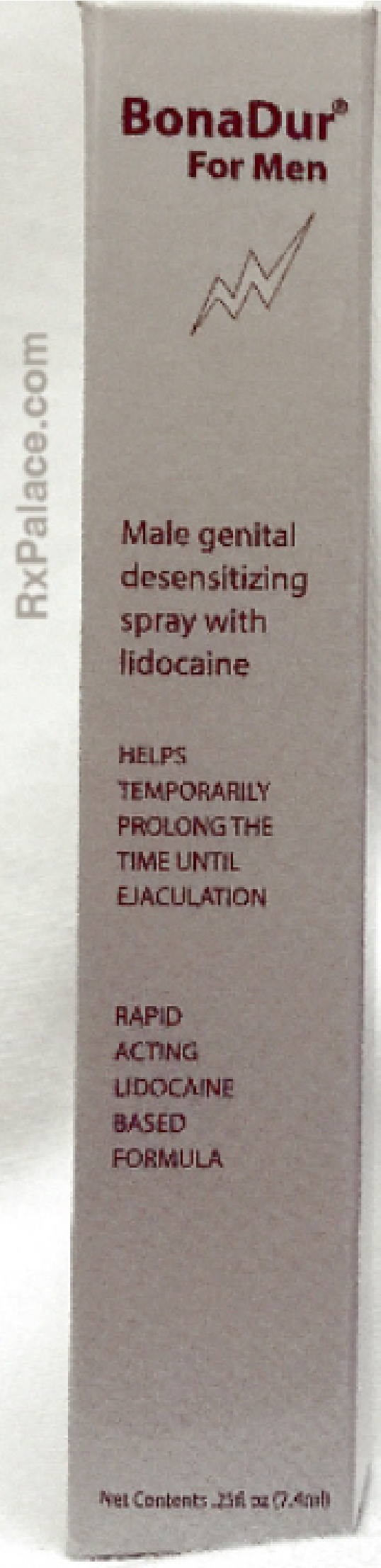 DRUG LABEL: BonaDur
NDC: 70582-999 | Form: SPRAY
Manufacturer: WebRx Pharmacy Palace
Category: otc | Type: HUMAN OTC DRUG LABEL
Date: 20181120

ACTIVE INGREDIENTS: LIDOCAINE HYDROCHLORIDE 10 mg/1 mg
INACTIVE INGREDIENTS: ALCOHOL; WATER; PEPPERMINT OIL; ANHYDROUS CITRIC ACID; THYMOL; SACCHARIN; PROPYLENE GLYCOL

BonaDur Spray for Men

Active Ingredient (per spray): Lidocaine approx. 10mg

Ask a doctor or pharmacist before use if

- You have liver problems.

Do not use if:

- You or your partner are allergic to lidocaine or topical anesthetics.
- Your partner is or may become pregnant.

- Keep out of reach of Children.
- If swallowed, get medical help or contact a Poison Control Center right away.

Stop use and ask a doctor

- if you or your partner develop a rash or irritation, such as burning or itching. If symptoms persist, consult a doctor.
- Premature ejaculation may be due to a condition requiring medical supervision. If this product, used as directed does not provide relief, discontinue use and consult a doctor.

Warnings:

For external use only.

When using this product

- Do not spray on broken, irritated or sensitive skin.
- Avoid contact with the eyes.

Indications and Usage

Helps in temporarily slowing the onset of ejaculation.

Male genital desensitizing spray with lidocaine

Directions:

Remove plastic cap. Press the actuator repeatedly until product dispenses to prime spray pump. Apply 3 or more sprays not to exceed 10 to the head and shaft of the penis 10 minutes before sexual intercourse or use as directed by a doctor. Recommended initial dosage: 3 sprays. Rub BonaDur into the skin of the penis until all of the product is absorbed. Wash product off after intercourse. Replace plastic cap after each use.

Other Information:

Keep away from fire and flame. Store at 20°-25° C (68°-77° F).

Inactive Ingredients:

Ethyl Alcohol, Propylene Glycol, Purified Water, Oil of Peppermint, Citric Acid, Thymol.

Questions?

Phone 1-877-797-2522 within the United States for reporting serious adverse events associated with use of the product.

PATIENT COUNSELING INFORMATION

To re-order this product or for product information please visit: www.BonaDur.com

OTC -Purpose

Anesthetic - Helps temporarily prolong the time until ejaculation

BonaDur® For Men

Male genital desensitizing spray with lidocaine

HELPS TEMPORARILY PROLONG THE TIME UNTIL EJACULATION

RAPID ACTING LIDOCAINE BASED FORMULA

Net Contents .25fl oz (7.4ml)